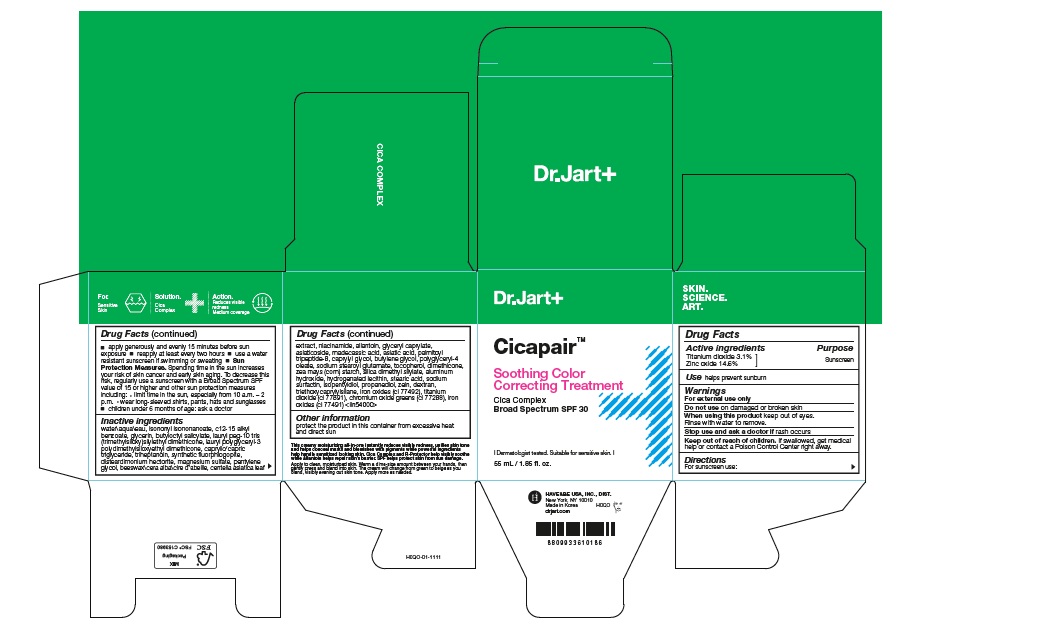 DRUG LABEL: Cicapair Soothing Color Correcting Treatment Cica Complex Broad Spectrum SPF 30
NDC: 49404-156 | Form: CREAM
Manufacturer: Have & Be Co., Ltd.
Category: otc | Type: HUMAN OTC DRUG LABEL
Date: 20250414

ACTIVE INGREDIENTS: TITANIUM DIOXIDE 31 mg/1 mL; ZINC OXIDE 146 mg/1 mL
INACTIVE INGREDIENTS: FERRIC OXIDE RED; PROPANEDIOL; ZEIN; SODIUM STEAROYL GLUTAMATE; CHROMIUM OXIDE GREENS; STEARIC ACID; TRIETHOXYCAPRYLYLSILANE; ALUMINUM HYDROXIDE; POLYGLYCERYL-4 OLEATE; TOCOPHEROL; HYDROGENATED SOYBEAN LECITHIN; ISOPENTYLDIOL; ASIATICOSIDE; MADECASSIC ACID; ZEA MAYS (CORN) STARCH; SILICA DIMETHYL SILYLATE; CAPRYLIC/CAPRIC TRIGLYCERIDE; PENTYLENE GLYCOL; DEXTRAN 40; DIMETHICONE; SODIUM SURFACTIN; FERRIC OXIDE YELLOW; WATER; C12-15 ALKYL BENZOATE; BUTYLOCTYL SALICYLATE; ISONONYL ISONONANOATE; GLYCERIN; LAURYL POLYGLYCERYL-3 POLYDIMETHYLSILOXYETHYL DIMETHICONE (4000 MPA.S); TRIHEPTANOIN; MAGNESIUM POTASSIUM ALUMINOSILICATE FLUORIDE; DISTEARDIMONIUM HECTORITE; MAGNESIUM SULFATE; BEESWAX; CENTELLA ASIATICA LEAF; NIACINAMIDE; ALLANTOIN; GLYCERYL CAPRYLATE; ASIATIC ACID; PALMITOYL TRIPEPTIDE-8; CAPRYLYL GLYCOL; BUTYLENE GLYCOL

Cicapair Soothing Color Correcting Treatment Cica Complex Broad Spectrum SPF 30

Active ingredients

Titanium dioxide 3.1%
Zinc oxide 14.6%

Purpose

Sunscreen

Use

helps prevent sunburn

Warnings

For external use only

Do not use on damaged or broken skin

When using this product keep out of eyes. Rinse with water to remove.

Stop use and ask a doctor if rash occurs

Keep out of reach of children. If product is swallowed, get medical help or contact a Poison Control Center right away.

Directions

- For sunscreen use:
- apply liberally 15 minutes before sun exposure
- reapply at least every two hours
- use a water resistant sunscreen if swimming or sweating
- Sun Protection Measures. Spending time in the sun increases your risk of skin cancer and early skin aging. To decrease this risk, regularly use a sunscreen with a Broad Spectrum SPF value of 15 or higher and other sun protection measures including:
- limit time in the sun, especially from 10 a.m.–2 p.m.
- wear long-sleeved shirts, pants, hats and sunglasses
- children under 6 months of age: ask a doctor

Other information

protect the product in this container from excessive heat and direct sun

Inactive ingredients

WATER\AQUA\EAU , ISONONYL ISONONANOATE , C12-15 ALKYL BENZOATE , GLYCERIN , BUTYLOCTYL SALICYLATE , LAURYL PEG-10 TRIS(TRIMETHYLSILOXY)SILYLETHYL DIMETHICONE , LAURYL POLYGLYCERYL-3 POLYDIMETHYLSILOXYETHYL DIMETHICONE , CAPRYLIC/CAPRIC TRIGLYCERIDE , TRIHEPTANOIN , SYNTHETIC FLUORPHLOGOPITE , DISTEARDIMONIUM HECTORITE , MAGNESIUM SULFATE , PENTYLENE GLYCOL , BEESWAX\CERA ALBA\CIRE D'ABEILLE , CENTELLA ASIATICA LEAF EXTRACT , NIACINAMIDE , ALLANTOIN , GLYCERYL CAPRYLATE , ASIATICOSIDE , MADECASSIC ACID , ASIATIC ACID , PALMITOYL TRIPEPTIDE-8 , CAPRYLYL GLYCOL , BUTYLENE GLYCOL , POLYGLYCERYL-4 OLEATE , SODIUM STEAROYL GLUTAMATE , TOCOPHEROL , DIMETHICONE , ZEA MAYS (CORN) STARCH , SILICA DIMETHYL SILYLATE , ALUMINUM HYDROXIDE , HYDROGENATED LECITHIN , STEARIC ACID , SODIUM SURFACTIN , ISOPENTYLDIOL , PROPANEDIOL , ZEIN , DEXTRAN , TRIETHOXYCAPRYLYLSILANE , IRON OXIDES (CI 77492) , TITANIUM DIOXIDE (CI 77891) , CHROMIUM OXIDE GREENS (CI 77288) , IRON OXIDES (CI 77491) <ILN54000>

PACKAGE LABEL

CicapairTM

Soothing Color
Correcting Treatment
Cica Complex
CicapairTM
Broad Spectrum SPF 30

55 mL / 1.85 fl. oz.